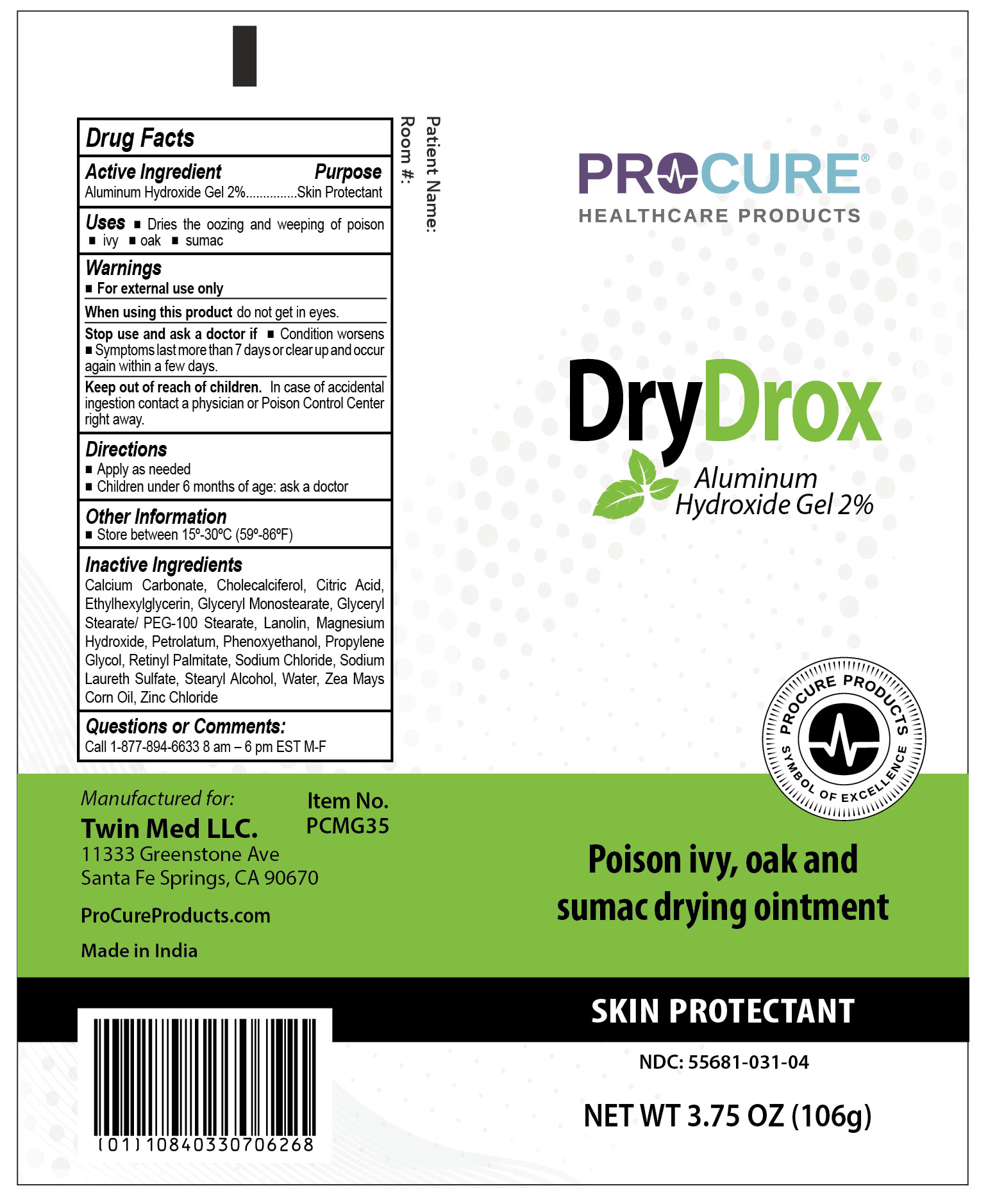 DRUG LABEL: ProCure DryDrox
NDC: 55681-031 | Form: OINTMENT
Manufacturer: Twin Med LLC
Category: otc | Type: HUMAN OTC DRUG LABEL
Date: 20250915

ACTIVE INGREDIENTS: ALUMINUM HYDROXIDE 2 g/100 g
INACTIVE INGREDIENTS: ZEA MAYS (CORN) OIL; GLYCERYL MONOSTEARATE; LANOLIN; MAGNESIUM HYDROXIDE; ETHYLHEXYLGLYCERIN; CALCIUM CARBONATE; CHOLECALCIFEROL; CITRIC ACID; GLYCERYL STEARATE/PEG-100 STEARATE; PETROLATUM; PHENOXYETHANOL; PROPYLENE GLYCOL; RETINYL PALMITATE; SODIUM CHLORIDE; SODIUM LAURETH SULFATE; STEARYL ALCOHOL; WATER; ZINC CHLORIDE

Active Ingredient

Aluminum Hydroxide Gel 2%

Purpose

Skin Protectant

Uses

- Dries the oozing and weeping of poison ivy, oak and sumac

Directions

- Apply as needed
- Children under 6 months of age: ask a doctor

Inactive Ingredients

Calcium Carbonate, Cholecalciferol, Citric Acid, Ethylhexylglycerin, Glyceryl Monostearate, Glyceryl Stearate/ PEG-100 Stearate, Lanolin, Magnesium Hydroxide, Petrolatum, Phenoxyethanol, Propylene Glycol, Retinyl Palmitate, Sodium Chloride, Sodium Laureth Sulfate,Stearyl Alcohol, Water, Zea Mays Corn Oil, Zinc Chloride

Warnings

For external use only

When using this product

When using this productdo not get into the eyes

Stop use and ask a doctor if

- Condition worsens
- Symptoms last more than 7 days or clear up and occur again within a few days

Keep out of reach of children.In case of accidental ingestion contact a physician or Poison Control Center right away.